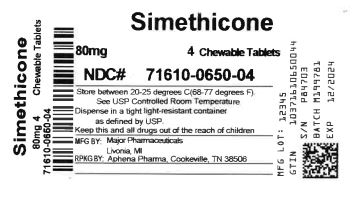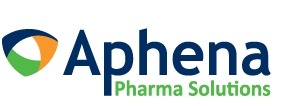 DRUG LABEL: Antiflatulent
NDC: 71610-650 | Form: TABLET, CHEWABLE
Manufacturer: Aphena Pharma Solutions - Tennessee, LLC
Category: otc | Type: HUMAN OTC DRUG LABEL
Date: 20250110

ACTIVE INGREDIENTS: DIMETHICONE 80 mg/1 1
INACTIVE INGREDIENTS: SUGARCANE; MALTODEXTRIN; DEXTROSE, UNSPECIFIED FORM; MAGNESIUM STEARATE; MICROCRYSTALLINE CELLULOSE; SORBITOL

Major Simethicone

ACTIVE INGREDIENT(in each tablet)

Simethicone 80 mg

PURPOSE

Antigas

USE(S)

relieves:

- pressure
- bloating
- symptoms referred to as gas

WARNINGS

.

KEEP OUT OF REACH OF CHILDREN

In case of overdose, get medical help or contact a Poison Control Center (1-800-222-1222) immediately.

DIRECTIONS

- chew 2 to 4 tablets thoroughly as needed after meals and at bedtime
- do not exceed 6 tablets per day unless directed by a physician

OTHER INFORMATION

- do not use if inner seal is broken
- store at room temperature
- avoid high humidity and excessive heat, above 40oC (104oF)

HOW SUPPLIED

Simethicone Chewable Tablets, 80 mg are white, round, tablets, debossed with "G and 103" on one side and are supplied as:

NDC 0904-7206-60 in bottle of 100 chewable tablets

Distributed by:

Major Pharmaceuticals

Livonia, MI 48152

INACTIVE INGREDIENTS

compressible sugar, dextrose, flavor, magnesium stearate, maltodextrin, microcrystalline cellulose, sorbitol.

QUESTIONS

Call (800) 616-2471

Repackaging Information

Please reference the How Suppliedsection listed above for a description of individual tablets. This drug product has been received by Aphena Pharma - TN in a manufacturer or distributor packaged configuration and repackaged in full compliance with all applicable cGMP regulations. The package configurations available from Aphena are listed below:

Count | 80 mg
4 | 71610-650-04

Store between 20°-25°C (68°-77°F). See USP Controlled Room Temperature. Dispense in a tight light-resistant container as defined by USP. Keep this and all drugs out of the reach of children.

Repackaged by:
Cookeville, TN 38506
20220519JK

PRINCIPAL DISPLAY PANEL - 80 mg

NDC 71610-650 - Simethicone 80 mg Chewable Tablet - Rx Only